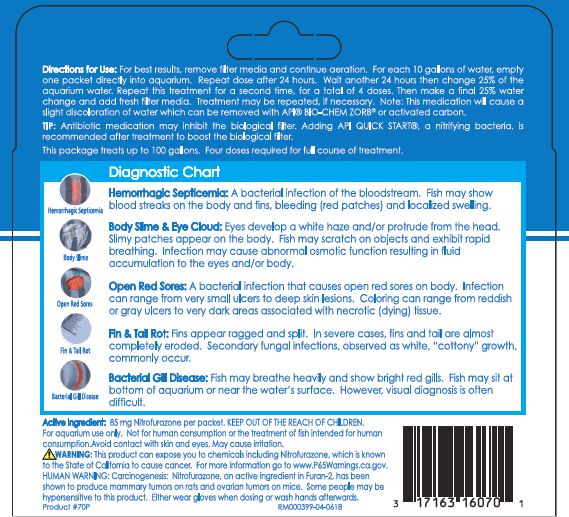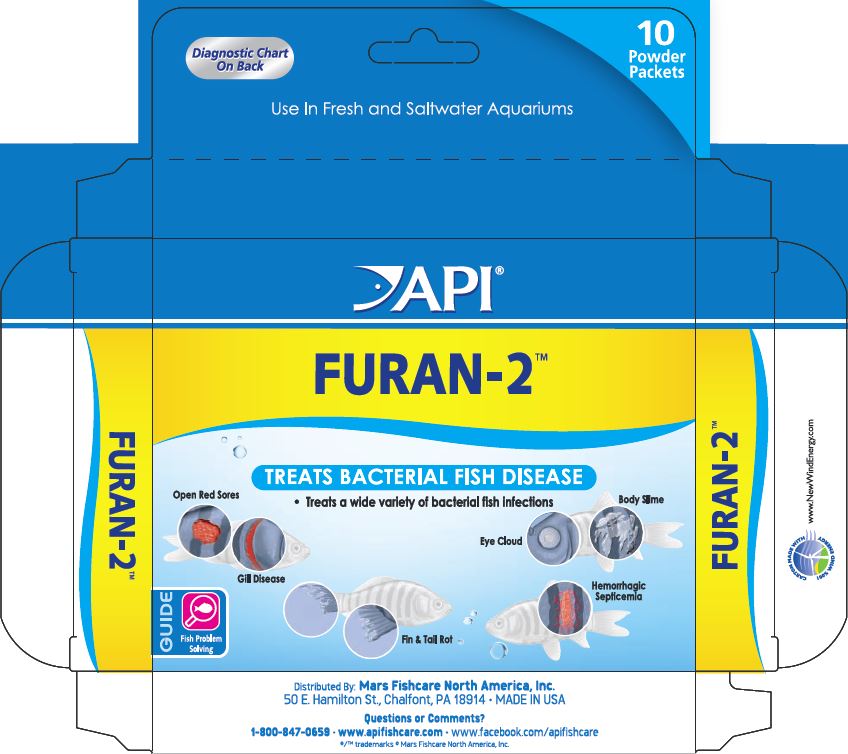 DRUG LABEL: API FURAN-2
NDC: 17163-070 | Form: POWDER
Manufacturer: MARS FISHCARE NORTH AMERICA, INC.
Category: animal | Type: OTC ANIMAL DRUG LABEL
Date: 20211229

ACTIVE INGREDIENTS: NITROFURAZONE  85 mg/2 g

Drug Label

Active ingredient: 85 mg Nitrofurazone per packet.

DOSAGE AND ADMINISTRATION

Directions for Use:

For best results, remove filter media and continue aeration

For each 10 gallons of water, empty one packet directly into aquarium.

Repeat dose after 24 hours. Wait another 24 hours then change 25% of the aquarium water.

Repeat this treatment for a second time, for a total of 4 doses.

Then male a final 25% water change and add fresh filter media.

Treatment may be repeated, if necessary.

Note: This medication will cause a slight discoloration of water which can be removed with API BIO-CHEM ZORB or activated carbon.

TIP: Antibiotic medication may inhibit the biological filter. Adding API QUICK START, a nitrifying bacteria,is recommended after treatment to boost the biological filter.

This package treats up to 100 gallons. Four doses required for full course of treatment.

INDICATIONS AND USAGE

Diagnostic Chart

Hemorrhagic Septicemia:

A bacterial infection of the bloodstream. Fish may show blood streaks on the body and fins, bleeding (red patches) and localized swelling.

Body Slime and Eye Cloud:

Eyes develop a white haze and/or protrude from the head. Slimy patches appear on the body. Fish may scratch on objects and exhibit rapid breathing. Infection may cause abnormal osmotic function resulting in fluid accumulation to the eyes and/or body.

Open Red Sores:

A bacterial infection that causes open red sores on the body. Infection can range from very small ulcers to deep skin lesions. Coloring can range from reddish or gray ulcers to very dark areas associated with necrotic (dying) tissue.

Fin and Tail Rot:

Fins appear ragged and split. In severe cases, fins and tail are almost completely eroded. Secondary fungal infections, observed as white, "cottony" growth, Commonly occur.

Bacterial Gill Disease:

Fishmay breathe heavily and show bright red gills. Fish may sit at bottom of aquarium or near the water's surface. However, visual diagnosis is often difficult.

WARNINGS AND PRECAUTIONS

KEEP OUT OF THE REACH OF CHILDREN.

For aquarium use only.

Not for human consumption or the treatment of fish intended for human consumption.

Avoid contact with skin and eyes.

May cause irritation.

! WARNING:

This product can expose you to chemicals including Nitrofurazone, which is known to the State of California to cause cancer.

For more information go to www.P65Warnings.ca.gov.

HUMAN WARNING:

Carcinogenesis: Nitrafurazone, an active ingredient in Furan-2, has been shown to produce mammary tumors on rats and ovarian tumors on mice.

Some people may be hypersensitive to this product.

Either wear gloves when dosing wash hands afterwards

PACKAGE LABEL

Diagnostic Chart

On Back

10 Powder

Packets

Use In Fresh and Saltwater Aquariums

AOI

FURAN-2

TREATS BACTERIAL FISH DISEASE

Treats a wide variety of bacterial fish infections

Open Red Sores

Gill Disease

Eye Cloud

Body Slime

Fin and Tail Rot

Hemorrhagic Septicemia

GUIDE

Fish Problem

Solving